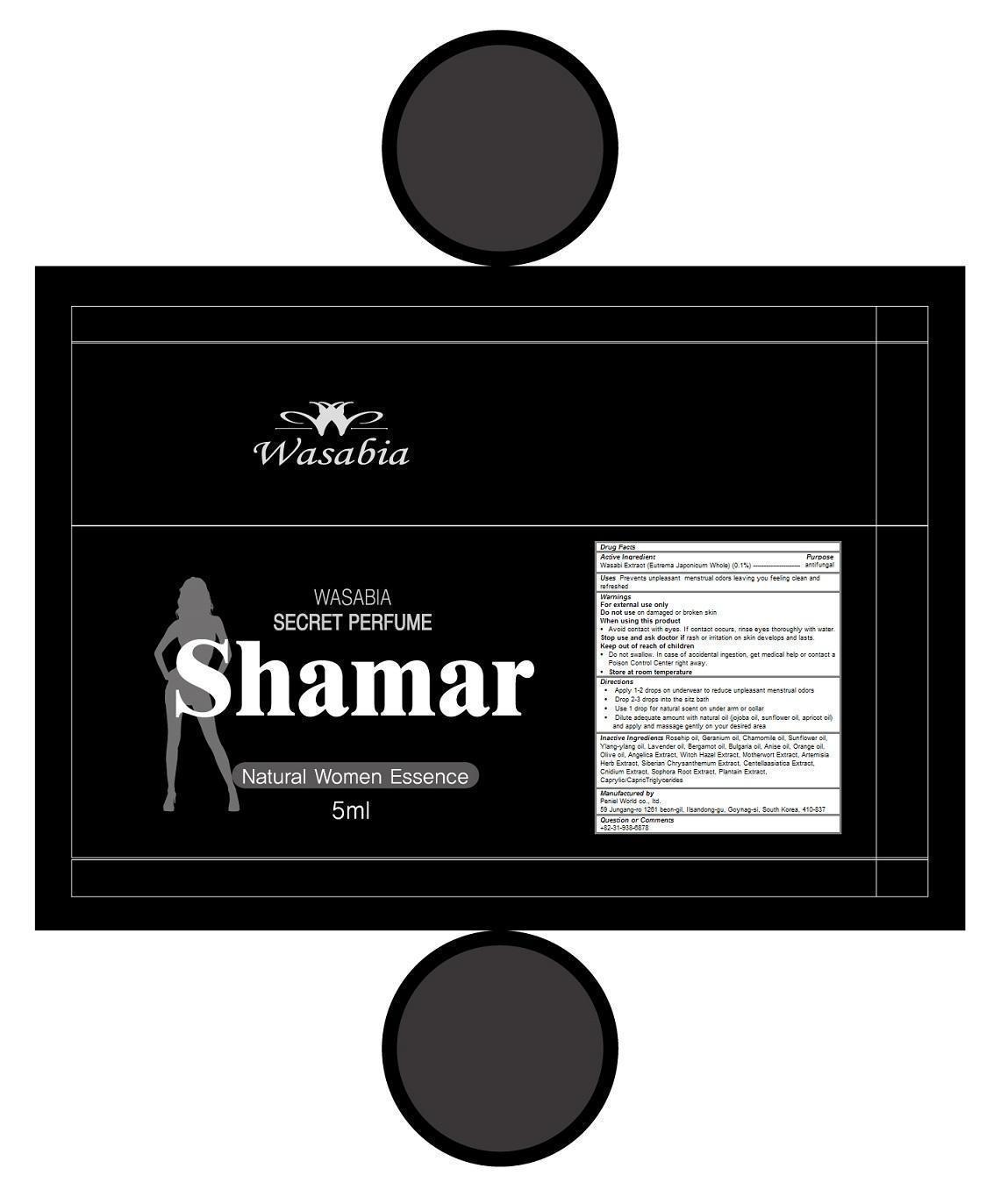 DRUG LABEL: Wasabia Secret Perfume - Shamar
NDC: 69708-101 | Form: LIQUID
Manufacturer: Peniel World co., ltd.
Category: otc | Type: HUMAN OTC DRUG LABEL
Date: 20150403

ACTIVE INGREDIENTS: EUTREMA JAPONICUM WHOLE 0.1 1/5 mL
INACTIVE INGREDIENTS: ROSA MOSCHATA OIL; PELARGONIUM GRAVEOLENS FLOWER OIL; CHAMOMILE FLOWER OIL; SUNFLOWER OIL; CANANGA OIL; LAVENDER OIL; BERGAMOT OIL; ANISE OIL; ORANGE OIL; OLIVE OIL; ANGELICA SEED; WITCH HAZEL; LEONURUS CARDIACA; CENTELLA ASIATICA; CNIDIUM MONNIERI FRUIT; SOPHORA FLAVESCENS ROOT; MUSA X PARADISIACA WHOLE; MEDIUM-CHAIN TRIGLYCERIDES

Wasabia Secret Perfume - Shamar